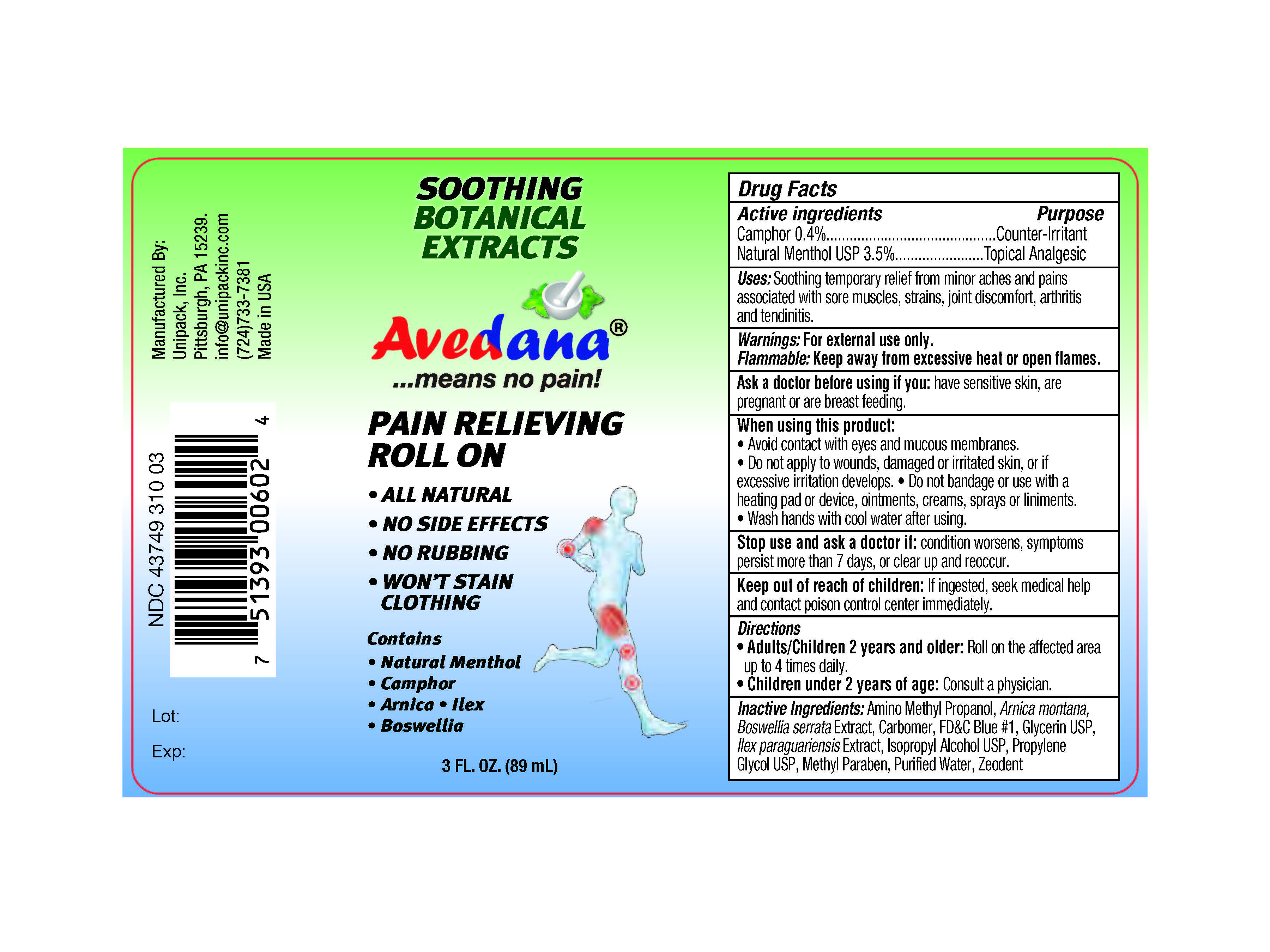 DRUG LABEL: Avedana Pain Relieving Roll On
NDC: 43749-310 | Form: GEL
Manufacturer: Unipack LLC
Category: otc | Type: HUMAN OTC DRUG LABEL
Date: 20220709

ACTIVE INGREDIENTS: MENTHOL 350 mg/1 mL; CAMPHOR (SYNTHETIC) 40 mg/1 mL
INACTIVE INGREDIENTS: WATER; CARBOMER 940; SILICON DIOXIDE; FD&C BLUE NO. 1; ISOPROPYL ALCOHOL; BOSWELLIA SERRATA RESIN OIL; ILEX PARAGUARIENSIS LEAF; ARNICA MONTANA; GLYCERIN; PROPYLENE GLYCOL; METHYLPARABEN; AMINOMETHYLPROPANOL

Avedana® Pain Relief Roll-On

Active ingredients

Active ingredients Purpose
Camphor 0.4%....................................................................Counter-Irritant
Natural Menthol USP 3.5%....................................................Topical Analgesic

Purpose

Active ingredients Purpose
Camphor 0.4%....................................................................Counter-Irritant
Natural Menthol USP 3.5%....................................................Topical Analgesic

Uses

Soothing temporary relief from minor aches and pains associated with sore muscles, strains, joint discomfort, arthritis and tendinitis.

Warnings

For external use only.

Flammable

Keep away from excessive heat or open flames.

Ask a doctor before using if you: have sensitive skin, are pregnant or are breast feeding.

When using this product:

- Avoid contact with eyes and mucous membranes.
- Do not apply to wounds, damaged or irritated skin, or if excessive irritation develops.
- Do not bandage or use with a heating pad or device, ointments, creams, sprays or liniments.
- Wash hands with cool water after using.

Stop use and ask a doctor if: condition worsens, symptoms persist more than 7 days, or clear up and reoccur.

Keep out of reach of children: If ingested, seek medical help and contact poison control center immediately.

Directions

-Adults/Children 2 years and older: Roll on the affected area up to 4 times daily.

-Children under 2 years of age: Consult a physician.

Inactive Ingredients:

Inactive Ingredients: Amino Methyl Propanol, Arnica montana, Boswellia serrata Extract, Carbomer, FD&C Blue #1, Glycerin USP, Ilex paraguariensis Extract, Isopropyl Alcohol USP, Propylene Glycol USP, Methyl Paraben, Purified Water, Zeodent

Directions

-Adults/Children 2 years and older: Roll on the affected area up to 4 times daily.
-Children under 2 years of age: Consult a physician.

Product Label

Avedana® Pain Relief Roll-On | 3 fl oz. | Bottle with Applicator.

- Easy to Use and Apply.
- Fast Relief from Pain.
- Back on Run like never before.